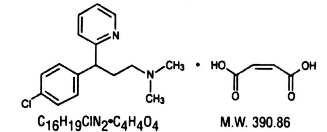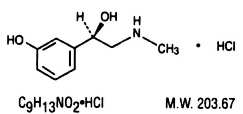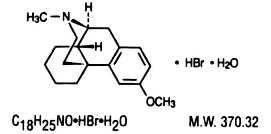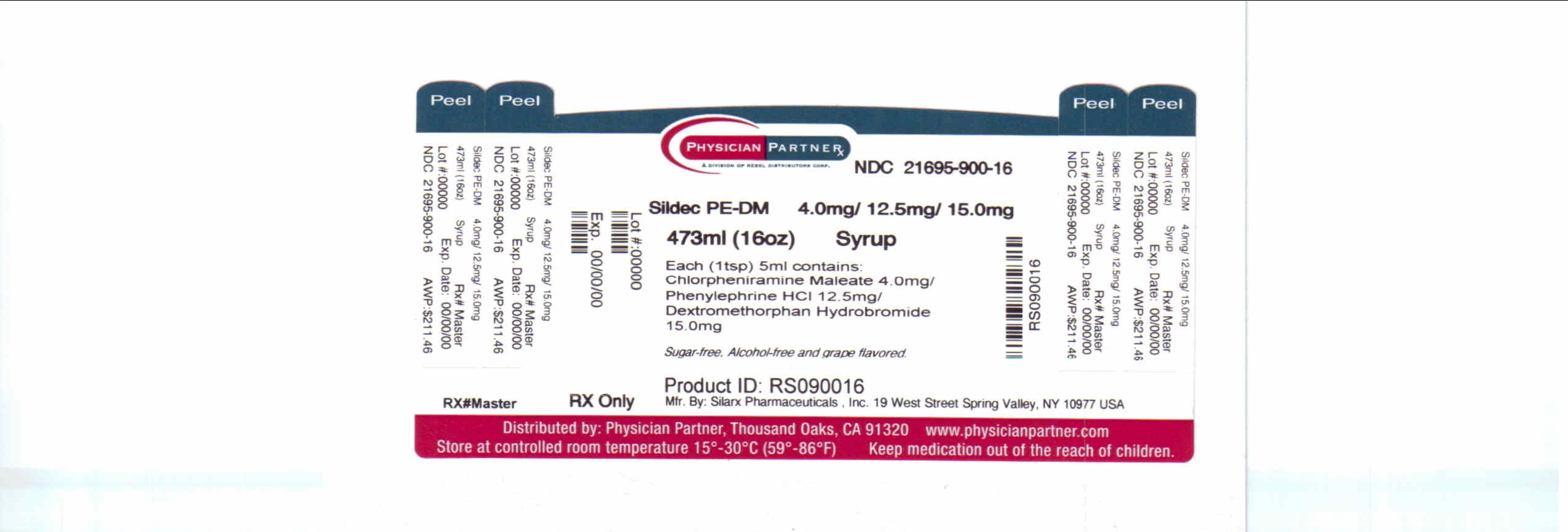 DRUG LABEL: Sildec PE DM
NDC: 21695-900 | Form: SYRUP
Manufacturer: Rebel Distributors Corp
Category: prescription | Type: HUMAN PRESCRIPTION DRUG LABEL
Date: 20110413

ACTIVE INGREDIENTS: CHLORPHENIRAMINE MALEATE 4 mg/5 mL; PHENYLEPHRINE HYDROCHLORIDE 12.5 mg/5 mL; DEXTROMETHORPHAN HYDROBROMIDE 15 mg/5 mL
INACTIVE INGREDIENTS: ANHYDROUS CITRIC ACID; D&C RED NO. 33; FD&C BLUE NO. 1; GLYCERIN; SODIUM BENZOATE; SACCHARIN SODIUM; SORBITOL; SODIUM CITRATE; WATER

CHLORPHENIRAMINE / PHENYLEPHRINE/ DEXTROMETHORPHAN Syrup (CPM/PE/DM Syrup)

DESCRIPTION

CPM/PE/DM Syrup is a sugar-free, alcohol-free, grape flavored syrup for oral administration for adults and for pediatric patients 2 years and older.

Each teaspoonful (5 mL) contains:
Chlorpheniramine maleate ………………. 4.0 mg
Phenylephrine hydrochloride ……………. 12.5 mg
Dextromethorphan hydrobromide ……….. 15.0 mg

Inactive ingredients: Citric acid, D&C Red No. 33, FD&C Blue No. 1, flavor, glycerin, purified water, sodium benzoate, sodium saccharin, and sorbitol. May contain sodium citrate.

Chlorpheniramine maleate is an antihistamine with the chemical name: 2-Pyridinepropanamine, y -(4-chlorophenyl)-N, N-dimethyl-, (Z)-2-butenedioate (1:1). Its chemical structure is as follows:

Phenylephrine hydrochloride is a mydriatic and a decongestant with the chemical name: (^-)-m-Hydroxy-α-[(methylamino)methyl]benzyl alcohol hydrochloride. Its chemical structure is as follows:

Dextromethorphan hydrobromide is an antitussive with the chemical name 3-Methoxy-17-methyl-9α, 13α, 14α - morphinan hydrobromide monohydrate. Its structure is as follows:

CLINICAL PHARMACOLOGY

Antihistaminic, decongestant and antitussive actions.

Chlorpheniramine maleate possesses H1 antihistaminic activity and mild anticholinergic and sedative effects. Peak plasma concentration is reached in 5 hours. Urinary excretion is the major route of elimination. The liver is assumed to be the major site of metabolic transformation.

Phenylephrine hydrochloride is an oral sympathomimetic amine that acts as a decongestant to respiratory tract mucous membranes. While its vasoconstrictor action is similar to that of ephedrine, phenylephrine has less pressor effect in normotensive adults. Serum half-life for phenylephrine is 6 to 8 hours. Acidic urine is associated with faster elimination of the drug. About one-half of the administered dose is excreted in the urine.

Dextromethorphan hydrobromide is a non-narcotic antitussive with effectiveness equal to codeine. It acts in the medulla oblongata to elevate the cough threshold. Dextromethorphan does not produce analgesia or induce tolerance, and has no potential for addiction. At usual doses, it will not depress respiration or inhibit ciliary activity. Dextromethorphan is rapidly metabolized with trace amounts of the parent compound in blood and urine. About one-half of the administered dose is excreted in the urine as conjugated metabolites.

INDICATIONS AND USAGE

For relief of coughs and upper respiratory symptoms, including nasal congestion, associated with allergy or the common cold.

CONTRAINDICATIONS

Patients with hypersensitivity or idiosyncrasy to any of its ingredients.

Sympathomimetic amines are contraindicated in patients with severe hypertension, severe coronary artery disease and patients on monoamine oxidase (MAO) inhibitor therapy. Antihistamines are contraindicated in patients with narrow angle glaucoma, urinary retention, peptic ulcer and during an asthma attack. Dextromethorphan should not be used in patients receiving a monoamine oxidase inhibitor (MAOI) or for 2 weeks after stopping the MAOI drug.

WARNINGS

Do not exceed recommended dosage.

Sympathomimetic amines should be used judiciously and sparingly in patients with hypertension, diabetes, ischemic heart disease, hyperthyroidism, increased intraocular pressure or prostatic hypertrophy (See CONTRAINDICATIONS). Sympathomimetic amines may produce CNS stimulation with convulsions or cardiovascular collapse with accompanying hypotension. The elderly (60 years and older) are more likely to exhibit adverse reactions. Antihistamines may cause excitability, especially in children. At doses higher than the recommended dose, nervousness, dizziness or sleeplessness may occur. Administration of dextromethorphan may be accompanied by histamine
release and should be used with caution in atopic children.

PRECAUTIONS

General: Before prescribing medication to suppress or modify cough, identify and provide therapy for the underlying cause of the cough and take caution that modification of cough does not increase the risk of clinical or physiologic complications. Dextromethorphan should be used with caution in sedated or debilitated patients and in patients confined to supine positions. Use with caution in patients with hypertension, heart disease, asthma, hyperthyroidism, increased intraocular pressure, diabetes mellitus and prostatic hypertrophy.

PATIENT COUNSELING INFORMATION

Information for Patients: Avoid alcohol and other CNS depressants while taking this product. Patients sensitive to antihistamines may experience moderate to severe drowsiness. Patients sensitive to sympathomimetic amines may notice mild CNS stimulation. Antihistamines may impair mental and physical abilities required for the performance of potentially hazardous tasks such as driving a vehicle or operating machinery. Patients should be warned accordingly.

DRUG INTERACTIONS

Drug Interactions: Antihistamines may enhance the effects of tricyclic antidepressants, barbiturates, alcohol and other CNS depressants. MAO inhibitors prolong and intensify the anticholinergic effects of antihistamines. Sympathomimetic amines may reduce the antihypertensive effects of reserpine, veratrum alkaloids, methyldopa and mecamylamines. Effects of sympathomimetics are increased with MAO inhibitors and beta-adrenergic blockers. The cough-suppressant action of dextromethorphan and narcotic antitussives are additive. Dextromethorphan is contraindicated with monoamine oxidase inhibitors (MAOI). (See CONTRAINDICATIONS section.)

PREGNANCY

Use in Pregnancy: Pregnancy Category C. Animal reproduction studies have not been conducted with CPM/PE/DM Syrup. It is not known whether these products can cause fetal harm when administered to a pregnant woman or affect reproduction capacity. Give to a pregnant woman only if clearly needed.

NURSING MOTHERS

Nursing Mothers: It is not known whether the drugs in CPM/PE/DM Syrup are excreted in human milk. Since many drugs are excreted in human milk and because of the potential for serious side effects in nursing infants, a decision should be made whether to discontinue nursing or discontinue the use of these products, taking into account the importance of the drug to the mother.

ADVERSE REACTIONS

Antihistamines may cause sedation, dizziness, diplopia, vomiting, diarrhea, dry mouth, headache, nervousness, nausea, anorexia, heartburn, weakness, polyuria and dysuria and, rarely, excitability in children. Urinary retention may occur in patients with prostatic hypertrophy. Sympathomimetic amines may cause convulsions, CNS stimulation, cardiac arrhythmia, respiratory difficulties, increased heart rate or blood pressure, hallucinations, tremors, nervousness, insomnia, pallor and dysuria. Dextromethorphan may cause drowsiness, dizziness and GI disturbance.

OVERDOSAGE

No information is available as to specific results of an overdose of CPM/PE/DM Syrup. The signs, symptoms and treatments described below are those of H1 antihistamine, ephedrine, and dextromethorphan overdose.

Symptoms: Should antihistamine effects predominate, central action constitutes the greatest danger. In the small child, predominant symptoms are excitation, hallucination, ataxia, incoordination, tremors, flushed face and fever. Convulsions, fixed and dilated pupils, coma and death may occur in severe cases. In the adult, fever and flushing are uncommon; excitement leading to convulsions and postictal depression is often preceded by drowsiness and coma. Respiration is usually not seriously depressed; blood pressure is usually stable.

Should sympathomimetic symptoms predominate, central effects include restlessness, dizziness, tremor, hyperactive reflexes, talkativeness, irritability and insomnia. Cardiovascular and renal effects include difficulty in micturition, headache, flushing, palpitation, cardiac arrhythmia, hypertension with subsequent hypotension and circulatory collapse. Gastrointestinal effects include dry mouth, metallic taste, anorexia, nausea, vomiting, diarrhea and abdominal cramps.

Dextromethorphan may cause respiratory depression with a large overdose.

Treatment: (a) Evacuate stomach as condition warrants. Activated charcoal may be useful. (b) Maintain a nonstimulating environment. (c) Monitor cardiovascular status. (d) Do not give stimulants. (e) Reduce fever with cool sponging. (f) Treat respiratory depression with naloxone if dextromethorphan toxicity is suspected. (g) Use sedatives or anticonvulsants to control CNS excitation and convulsions. (h) Physostigmine may reverse anticholinergic symptoms. (i) Ammonium chloride may acidify the urine to increase urinary excretion of phenylephrine. (j) Further care is symptomatic and supportive.

DOSAGE AND ADMINISTRATION

CHLORPHENIRAMINE / PHENYLEPHRINE/ DEXTROMETHORPHAN Syrup (CPM/PE/DM Syrup) Adults and Children 12 years of age and older: 1 teaspoonful (5 mL) every 4 to 6 hours, not to exceed 6 teaspoonfuls in 24 hours. Children 6 to under 12 years of age: 1/2 teaspoonful (2.5 mL) every 4 to 6 hours, not to exceed 3 teaspoonfuls in 24 hours. Children 2 to under 6 years of age: 1/4 teaspoonful (1.25 mL) every 4 to 6 hours, not to exceed 1.5 teaspoonfuls in 24 hours. Not recommended for use in children under 2 years of age.

In mild cases or in particularly sensitive patients, less frequent or reduced doses may be appropriate and adequate.

HOW SUPPLIED

CHLORPHENIRAMINE / PHENYLEPHRINE/ DEXTROMETHORPHAN Syrup (CPM/PE/DM Syrup) CPM/PE/DM Syrup is sugar-free, alcohol-free, and grape flavored.

It is available in bottles of 16 fluid ounce (473 mL) bottles - NDC 21695-900-16.

Dispense in a tight, light-resistant container as defined in USP with a child resistant closure.

STORAGE REQUIREMENTS

Store at Controlled Room Temperature between 20°-25°C (68°-77°F); excursions permitted to 15°- 30°C (59°-86°F) [See USP Controlled Room Temperature]. Avoid exposure to heat. Keep tightly closed.

KEEP THIS AND ALL DRUGS OUT OF THE REACH OF CHILDREN. In case of accidental overdose, seek professional assistance or contact a Poison Control Center immediately.

Manufactured by:
Silarx Pharmaceuticals, Inc.
Spring Valley, NY 10977
USA

Repackaged by:

Rebel Distributors Corp

Thousand Oaks, CA 91320